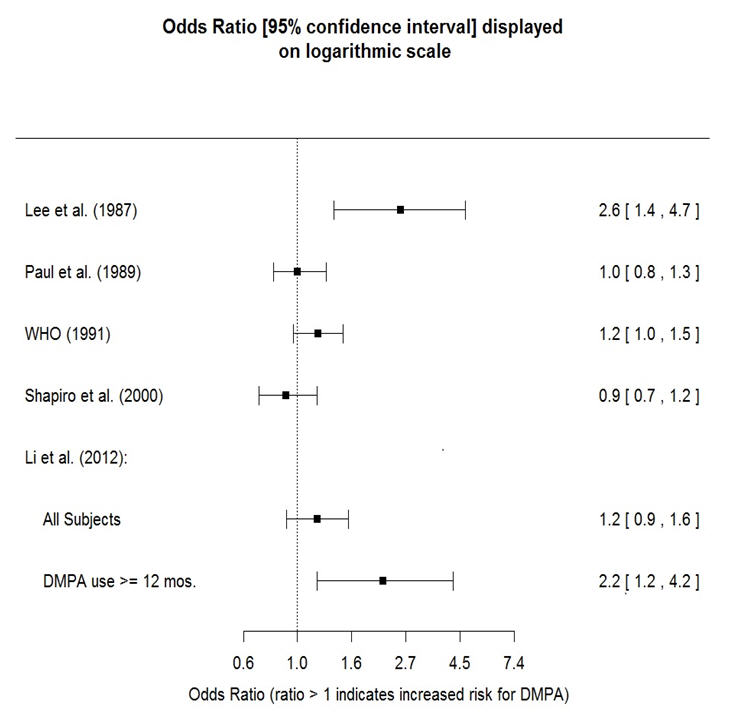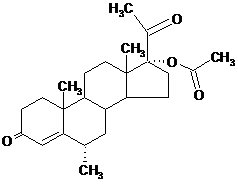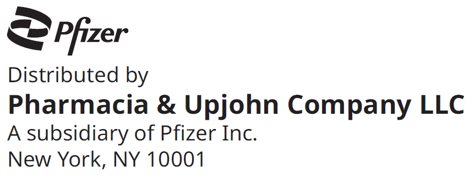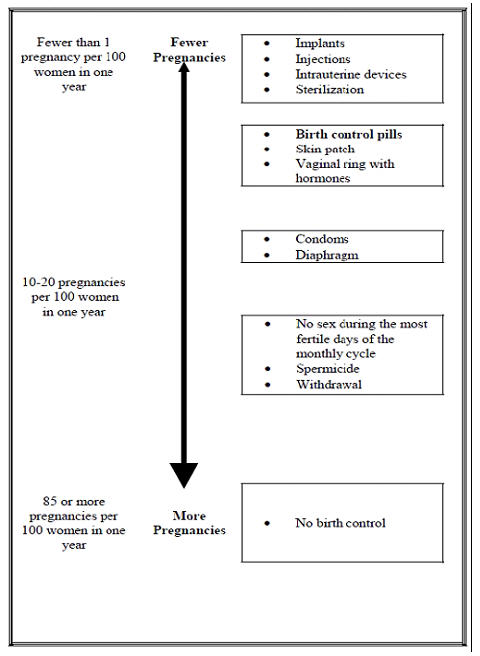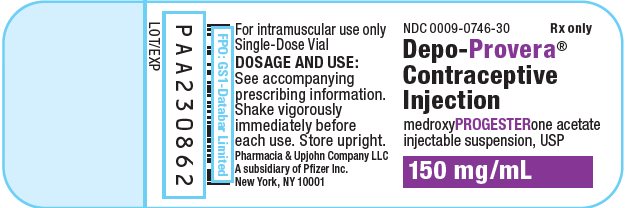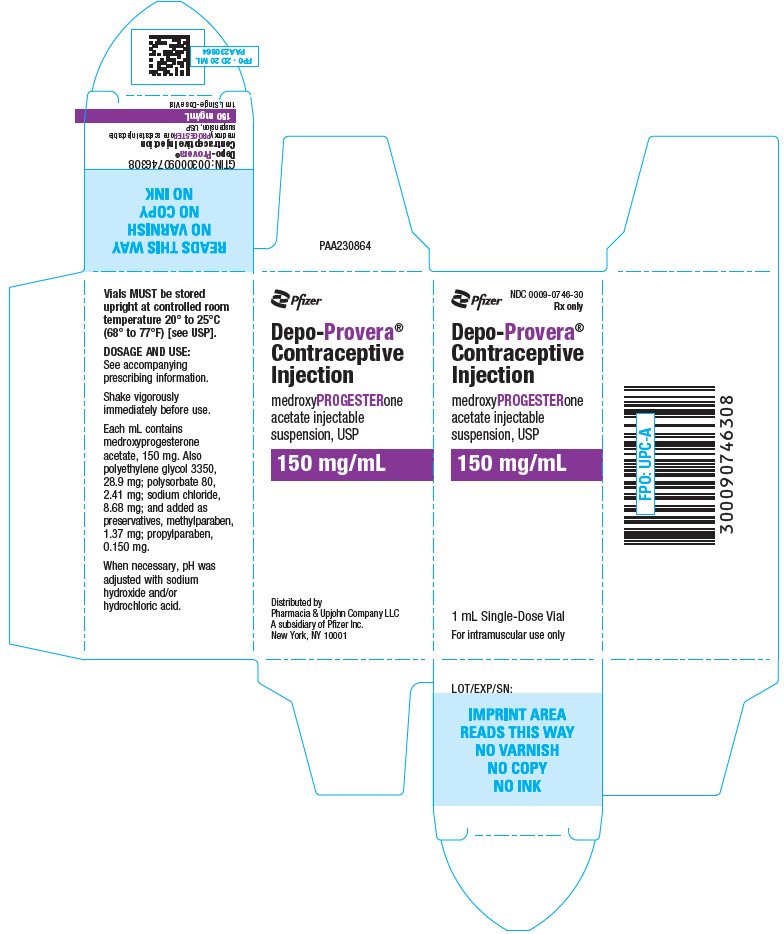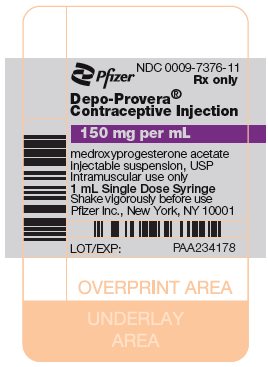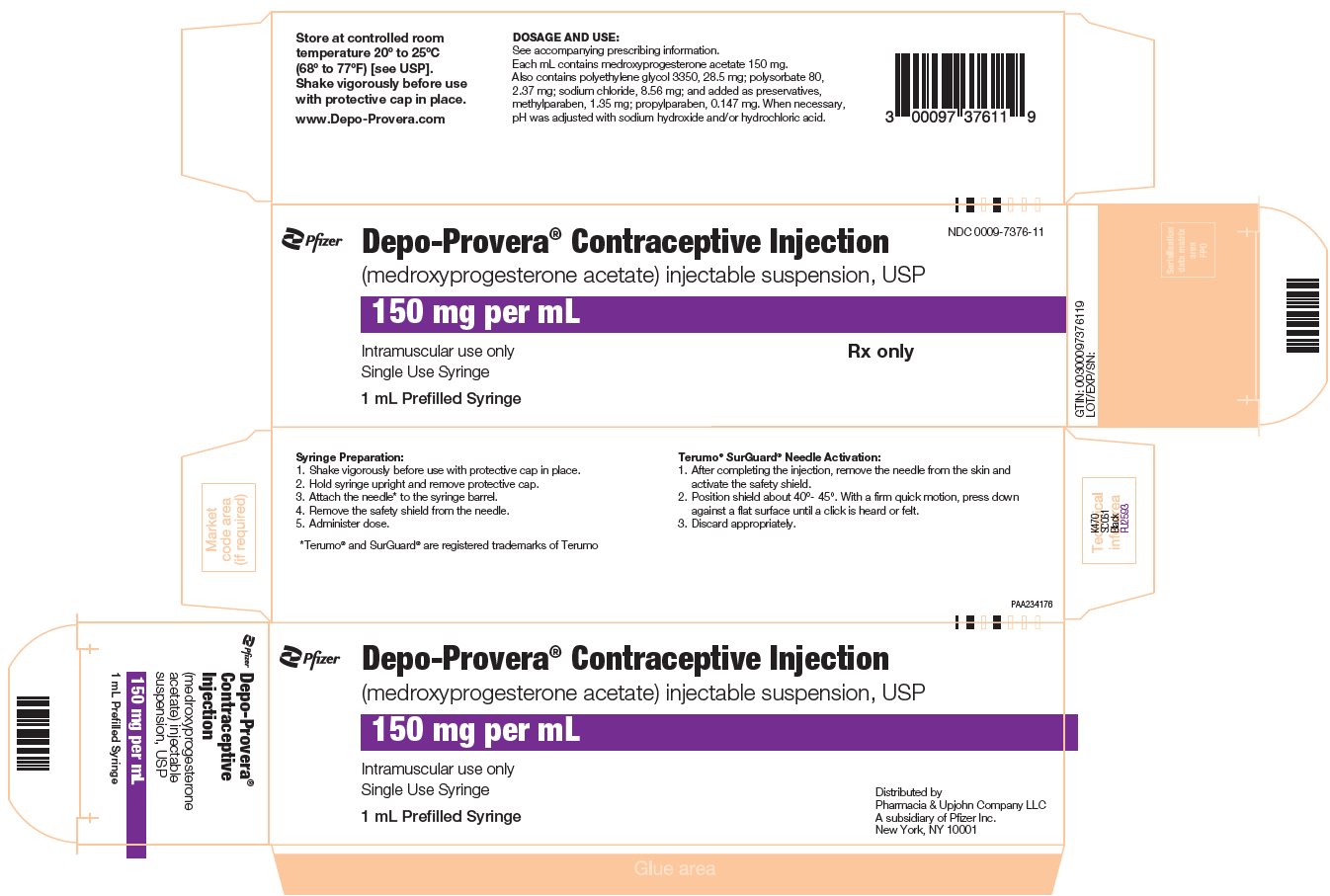 DRUG LABEL: Depo-Provera
NDC: 0009-0746 | Form: INJECTION, SUSPENSION
Manufacturer: Pharmacia & Upjohn Company LLC
Category: prescription | Type: HUMAN PRESCRIPTION DRUG LABEL
Date: 20251218

ACTIVE INGREDIENTS: MEDROXYPROGESTERONE ACETATE 150 mg/1 mL
INACTIVE INGREDIENTS: POLYETHYLENE GLYCOL 3350 28.9 mg/1 mL; POLYSORBATE 80 2.41 mg/1 mL; SODIUM CHLORIDE 8.68 mg/1 mL; METHYLPARABEN 1.37 mg/1 mL; PROPYLPARABEN 0.15 mg/1 mL; WATER; SODIUM HYDROXIDE; HYDROCHLORIC ACID

HIGHLIGHTS OF PRESCRIBING INFORMATION

These highlights do not include all the information needed to use DEPO-PROVERA CI safely and effectively. See full prescribing information for DEPO-PROVERA CI.
DEPO-PROVERA CI (medroxyprogesterone acetate) injectable suspension, for intramuscular use
Initial U.S. Approval: 1959

WARNING: LOSS OF BONE MINERAL DENSITY

See full prescribing information for complete boxed warning.

- Women who use Depo-Provera Contraceptive Injection (Depo-Provera CI) may lose significant bone mineral density. Bone loss is greater with increasing duration of use and may not be completely reversible. (5.1)
- It is unknown if use of Depo-Provera CI during adolescence or early adulthood, a critical period of bone accretion, will reduce peak bone mass and increase the risk for osteoporotic fracture in later life. (5.1)
- Depo-Provera CI is not recommended as a long-term (i.e., longer than 2 years) birth control method unless other options are considered inadequate. (1, 5.1)

RECENT MAJOR CHANGES

Warnings and Precautions, Meningioma (5.4) | 12/2025

1 INDICATIONS AND USAGE

Depo-Provera CI is a progestin indicated for use by females of reproductive potential to prevent pregnancy. (1)

Limitations of Use:

The use of Depo-Provera CI is not recommended as a long-term (i.e., longer than 2 years) birth control method unless other options are considered inadequate. (1, 5.1)

2 DOSAGE AND ADMINISTRATION

The recommended dose is 150 mg of Depo-Provera CI every 3 months (13 weeks) administered by deep, intramuscular (IM) injection in the gluteal or deltoid muscle. (2.1)

3 DOSAGE FORMS AND STRENGTHS

- Vials containing sterile aqueous suspension: 150 mg per mL (3)
- Prefilled syringes: prefilled syringes are available packaged with 22-gauge x 1 1/2 inch Terumo® SurGuard™ Needles. (3)

4 CONTRAINDICATIONS

- Active thrombophlebitis, or current or past history of thromboembolic disorders, or cerebral vascular disease. (4)
- Known or suspected malignancy of breast. (4)
- Known hypersensitivity to Depo-Provera CI (medroxyprogesterone acetate or any of its other ingredients). (4)
- Significant liver disease. (4)
- Undiagnosed vaginal bleeding. (4)

5 WARNINGS AND PRECAUTIONS

- Thromboembolic Disorders: Discontinue Depo-Provera CI in patients who develop thrombosis. (5.2)
- Cancer Risks: Monitor women with a strong family history of breast cancer carefully. (5.3)
- Meningioma: Discontinue Depo-Provera CI if meningioma is diagnosed. Monitor patients for signs and symptoms of meningioma. (5.4)
- Ectopic Pregnancy: Consider ectopic pregnancy if a woman using Depo-Provera CI becomes pregnant or complains of severe abdominal pain. (5.5)
- Anaphylaxis and Anaphylactoid Reactions: Provide emergency medical treatment. (5.6)
- Liver Function: Discontinue Depo-Provera CI if jaundice or disturbances of liver function develop. (5.8)
- Carbohydrate Metabolism: Monitor diabetic patients carefully. (5.13)

6 ADVERSE REACTIONS

Most common adverse reactions (incidence >5%): menstrual irregularities (bleeding or spotting) 57% at 12 months, 32% at 24 months, abdominal pain/discomfort 11%, weight gain >10 lb at 24 months 38%, dizziness 6%, headache 17%, nervousness 11%, decreased libido 6%. (6.1)

To report SUSPECTED ADVERSE REACTIONS, contact Pfizer Inc. at 1-800-438-1985 or FDA at 1-800-FDA-1088 or www.fda.gov/medwatch.

7 DRUG INTERACTIONS

Drugs or herbal products that induce certain enzymes, including CYP3A4, may decrease the effectiveness of contraceptive drug products. Counsel patients to use a back-up method or alternative method of contraception when enzyme inducers are used with Depo-Provera CI. (7.1)

8 USE IN SPECIFIC POPULATIONS

- Pregnancy: Discontinue if pregnancy occurs. (8.1)
- Lactation: Detectable amounts of drug have been identified in the milk of mothers receiving Depo-Provera CI. (8.2)
- Pediatric Patients: Depo-Provera CI is not indicated before menarche. (8.4)

FULL PRESCRIBING INFORMATION

WARNING: LOSS OF BONE MINERAL DENSITY

- Women who use Depo-Provera Contraceptive Injection (Depo-Provera CI) may lose significant bone mineral density. Bone loss is greater with increasing duration of use and may not be completely reversible [see Warnings and Precautions (5.1)].
- It is unknown if use of Depo-Provera CI during adolescence or early adulthood, a critical period of bone accretion, will reduce peak bone mass and increase the risk for osteoporotic fracture in later life [see Warnings and Precautions (5.1)].
- Depo-Provera CI is not recommended as a long-term (i.e., longer than 2 years) birth control method unless other options are considered inadequate [see Indications and Usage (1) and Warnings and Precautions (5.1)].

1 INDICATIONS AND USAGE

Depo-Provera CI is indicated for use by females of reproductive potential to prevent pregnancy.

Limitations of Use:

The use of Depo-Provera CI is not recommended as a long-term (i.e., longer than 2 years) birth control method unless other options are considered inadequate [see Dosage and Administration (2.1) and Warnings and Precautions (5.1)].

2 DOSAGE AND ADMINISTRATION

2.1 Prevention of Pregnancy

Both the 1 mL vial and the 1 mL prefilled syringe of Depo-Provera CI should be vigorously shaken just before use to ensure that the dose being administered represents a uniform suspension.

The recommended dose is 150 mg of Depo-Provera CI every 3 months (13 weeks) administered by deep intramuscular (IM) injection using strict aseptic technique in the gluteal or deltoid muscle, rotating the sites with every injection. As with any IM injection, to avoid an inadvertent subcutaneous injection, body habitus should be assessed prior to each injection to determine if a longer needle is necessary particularly for gluteal IM injection.

Use for longer than 2 years is not recommended (unless other birth control methods are considered inadequate) due to the impact of long-term Depo-Provera CI treatment on bone mineral density (BMD) [see Warnings and Precautions (5.1)]. Dosage does not need to be adjusted for body weight [see Clinical Studies (14.1)].

To ensure the patient is not pregnant at the time of the first injection, the first injection should be given ONLY during the first 5 days of a normal menstrual period or within the first 5-days post‑partum. In post‑partum mothers who exclusively breastfeed, administer Depo‑Provera CI during or after the sixth post‑partum week. If the time interval between injections is greater than 13 weeks, the physician should determine that the patient is not pregnant before administering the drug. The efficacy of Depo-Provera CI depends on adherence to the dosage schedule of administration.

2.2 Switching from Other Methods of Contraception

When switching from other contraceptive methods, Depo-Provera CI should be given in a manner that ensures continuous contraceptive coverage based upon the mechanism of action of both methods, (e.g., patients switching from oral contraceptives should have their first injection of Depo-Provera CI on the day after the last active tablet or at the latest, on the day following the final inactive tablet).

3 DOSAGE FORMS AND STRENGTHS

Sterile Aqueous suspension: 150 mg/mL

Prefilled syringes are available packaged with 22-gauge x 1 1/2 inch Terumo® SurGuard™ Needles.

4 CONTRAINDICATIONS

The use of Depo-Provera CI is contraindicated in the following conditions:

- Active thrombophlebitis, or current or history of thromboembolic disorders, or cerebral vascular disease [see Warnings and Precautions (5.2)].
- Known or suspected malignancy of breast [see Warnings and Precautions (5.3)].
- Known hypersensitivity to Depo-Provera CI (medroxyprogesterone acetate) or any of its other ingredients [see Warnings and Precautions (5.6)].
- Significant liver disease [see Warnings and Precautions (5.8)].
- Undiagnosed vaginal bleeding [see Warnings and Precautions (5.11)].

5 WARNINGS AND PRECAUTIONS

5.1 Loss of Bone Mineral Density

Use of Depo-Provera CI reduces serum estrogen levels and is associated with significant loss of bone mineral density (BMD). This loss of BMD is of particular concern during adolescence and early adulthood, a critical period of bone accretion. It is unknown if use of Depo-Provera CI by younger women will reduce peak bone mass and increase the risk for osteoporotic fracture in later life.

A study to assess the reversibility of loss of BMD in adolescents was conducted with Depo-Provera CI. After discontinuing Depo-Provera CI in these adolescents, mean BMD loss at the total hip and femoral neck did not fully recover by 5 years (60 months) post-treatment in the sub-group of adolescents who were treated for more than 2 years [see Clinical Studies (14.3)]. Similarly, in adults, there was only partial recovery of mean BMD at the total hip, femoral neck, and lumbar spine towards baseline by 2 years post-treatment [see Clinical Studies (14.2)].

The use of Depo-Provera CI is not recommended as a long-term (i.e., longer than 2 years) birth control method unless other options are considered inadequate. BMD should be evaluated when a woman needs to continue to use Depo-Provera CI long-term. In adolescents, interpretation of BMD results should take into account patient age and skeletal maturity.

Other birth control methods should be considered in the risk/benefit analysis for the use of Depo-Provera CI in women with osteoporosis risk factors. Depo-Provera CI can pose an additional risk in patients with risk factors for osteoporosis (e.g., metabolic bone disease, chronic alcohol and/or tobacco use, anorexia nervosa, strong family history of osteoporosis or chronic use of drugs that can reduce bone mass such as anticonvulsants or corticosteroids).

5.2 Thromboembolic Disorders

There have been reports of serious thrombotic events in women using Depo-Provera CI (150 mg). However, Depo-Provera CI has not been causally associated with the induction of thrombotic or thromboembolic disorders. Any patient who develops thrombosis while undergoing therapy with Depo-Provera CI should discontinue treatment unless she has no other acceptable options for birth control.

Do not re-administer Depo-Provera CI pending examination if there is a sudden partial or complete loss of vision or if there is a sudden onset of proptosis, diplopia, or migraine. Do not re-administer if examination reveals papilledema or retinal vascular lesions.

5.3 Cancer Risks

Breast Cancer

Women who have or have had a history of breast cancer should not use hormonal contraceptives, including Depo-Provera CI, because breast cancer may be hormonally sensitive [see Contraindications (4)]. Women with a strong family history of breast cancer should be monitored with particular care.

The results of five large case-control studies assessing the association between depo-medroxyprogesterone acetate (DMPA) use and the risk of breast cancer are summarized in Figure 1. Three of the studies suggest a slightly increased risk of breast cancer in the overall population of users; these increased risks were statistically significant in one study. One recent US study^1 evaluated the recency and duration of use and found a statistically significantly increased risk of breast cancer in recent users (defined as last use within the past five years) who used DMPA for 12 months or longer; this is consistent with results of a previous study^2.

Figure 1. Risk estimates for breast cancer in DMPA users

Odds ratio estimates were adjusted for the following covariates:

Lee et al. (1987): age, parity, and socioeconomic status.

Paul et al. (1989): age, parity, ethnic group, and year of interview.

WHO (1991): age, center, and age at first live birth.

Shapiro et al. (2000): age, ethnic group, socioeconomic status, and any combined estrogen/progestogen oral contraceptive use.

Li et al. (2012): age, year, BMI, duration of OC use, number of full-term pregnancies, family history of breast cancer, and history of screening mammography.

Based on the published SEER-18 2011 incidence rate (age-adjusted to the 2000 US Standard Population) of breast cancer for US women, all races, age 20 to 49 years, a doubling of risk would increase the incidence of breast cancer in women who use Depo-Provera CI from about 72 to about 144 cases per 100,000 women.

Cervical Cancer

A statistically nonsignificant increase in relative risk (RR) estimates of invasive squamous-cell cervical cancer has been associated with the use of Depo-Provera CI in women who were first exposed before the age of 35 years (RR 1.22 to 1.28 and 95% CI 0.93 to 1.70). The overall, nonsignificant RR of invasive squamous-cell cervical cancer in women who ever used Depo-Provera CI was estimated to be 1.11 (95% CI 0.96 to 1.29). No trends in risk with duration of use or times since initial or most recent exposure were observed.

Other Cancers

Long-term case-controlled surveillance of users of Depo-Provera CI found no overall increased risk of ovarian or liver cancer.

5.4 Meningioma

Cases of meningiomas have been reported following repeated administration of medroxyprogesterone acetate, primarily with long term use. Monitor patients on Depo-Provera CI for signs and symptoms of meningioma. Discontinue Depo-Provera CI if a meningioma is diagnosed.

5.5 Ectopic Pregnancy

Be alert to the possibility of an ectopic pregnancy among women using Depo-Provera CI who become pregnant or complain of severe abdominal pain.

5.6 Anaphylaxis and Anaphylactoid Reaction

Anaphylaxis and anaphylactoid reaction have been reported with the use of Depo-Provera CI. Institute emergency medical treatment if an anaphylactic reaction occurs.

5.7 Injection Site Reactions

Injection site reactions have been reported with use of Depo-Provera CI [see Adverse Reactions (6.2)]. Persistent injection site reactions may occur after administration of Depo-Provera CI due to inadvertent subcutaneous administration or release of the drug into the subcutaneous space while removing the needle [see Dosage and Administration (2.1)].

5.8 Liver Function

Discontinue Depo-Provera CI use if jaundice or acute or chronic disturbances of liver function develop. Do not resume use until markers of liver function return to normal and Depo-Provera CI causation has been excluded.

5.9 Convulsions

There have been a few reported cases of convulsions in patients who were treated with Depo-Provera CI. Association with drug use or pre-existing conditions is not clear.

5.10 Depression

Monitor patients who have a history of depression and do not re-administer Depo-Provera CI if depression recurs.

5.11 Bleeding Irregularities

Most women using Depo-Provera CI experience disruption of menstrual bleeding patterns. Altered menstrual bleeding patterns include amenorrhea, irregular or unpredictable bleeding or spotting, prolonged spotting or bleeding, and heavy bleeding. Rule out the possibility of organic pathology if abnormal bleeding persists or is severe, and institute appropriate treatment.

As women continue using Depo-Provera CI, fewer experience irregular bleeding and more experience amenorrhea. In clinical studies of Depo-Provera CI, by month 12 amenorrhea was reported by 55% of women, and by month 24, amenorrhea was reported by 68% of women using Depo-Provera CI.

5.12 Weight Gain

Women tend to gain weight while on therapy with Depo-Provera CI. From an initial average body weight of 136 lb, women who completed 1 year of therapy with Depo-Provera CI gained an average of 5.4 lb. Women who completed 2 years of therapy gained an average of 8.1 lb. Women who completed 4 years gained an average of 13.8 lb. Women who completed 6 years gained an average of 16.5 lb. Two percent of women withdrew from a large-scale clinical trial because of excessive weight gain.

5.13 Carbohydrate Metabolism

A decrease in glucose tolerance has been observed in some patients on Depo-Provera CI treatment. Monitor diabetic patients carefully while receiving Depo-Provera CI.

5.14 Fluid Retention

Because progestational drugs including Depo-Provera CI may cause some degree of fluid retention, monitor patients with conditions that might be influenced by this condition, such as epilepsy, migraine, asthma, and cardiac or renal dysfunction.

5.15 Return of Fertility

Return to ovulation and fertility is likely to be delayed after stopping Depo-Provera CI. In a large US study of women who discontinued use of Depo-Provera CI to become pregnant, data are available for 61% of them. Of the 188 women who discontinued the study to become pregnant, 114 became pregnant. Based on Life-Table analysis of these data, it is expected that 68% of women who do become pregnant may conceive within 12 months, 83% may conceive within 15 months, and 93% may conceive within 18 months from the last injection. The median time to conception for those who do conceive is 10 months following the last injection with a range of 4 to 31 months, and is unrelated to the duration of use. No data are available for 39% of the patients who discontinued Depo-Provera CI to become pregnant and who were lost to follow-up or changed their mind.

5.16 Sexually Transmitted Infections

Patients should be counseled that Depo-Provera CI does not protect against HIV infection (AIDS) and other sexually transmitted infections.

5.17 Monitoring

A woman who is taking hormonal contraceptive should have a yearly visit with her healthcare professional for a blood pressure check and for other indicated healthcare.

5.18 Interference with Laboratory Tests

The use of Depo-Provera CI may change the results of some laboratory tests, such as coagulation factors, lipids, glucose tolerance, and binding proteins [see Drug Interactions (7.2)].

6 ADVERSE REACTIONS

The following important adverse reactions observed with the use of Depo-Provera CI are discussed in greater detail in the Warnings and Precautions section (5):

- Loss of Bone Mineral Density [see Warnings and Precautions (5.1)]
- Thromboembolic disease [see Warnings and Precautions (5.2)]
- Breast Cancer [see Warnings and Precautions (5.3)]
- Anaphylaxis and Anaphylactoid Reactions [see Warnings and Precautions (5.6)]
- Bleeding Irregularities [see Warnings and Precautions (5.11)]
- Weight Gain [see Warnings and Precautions (5.12)]

6.1 Clinical Trials Experience

Clinical trials are conducted under widely varying conditions, therefore, adverse reaction rates observed in the clinical studies of a drug cannot be directly compared to rates in the clinical trials of another drug and may not reflect the rates observed in practice.

In the two clinical trials with Depo-Provera CI, over 3,900 women, who were treated for up to 7 years, reported the following adverse reactions, which may or may not be related to the use of Depo-Provera CI. The population studied ranges in age from 15 to 51 years, of which 46% were White, 50% Non-White, and 4.9% Unknown race. The patients received 150 mg Depo-Provera CI every 3-months (90 days). The median study duration was 13 months with a range of 1-84 months. Fifty‑eight percent of patients remained in the study after 13 months and 34% after 24 months.

Table 1. Adverse Reactions that Were Reported by More than 5% of Subjects
Body System [Body System represented from COSTART medical dictionary.] | Adverse Reactions [Incidence (%)]
Body as a Whole | Headache (16.5%); Abdominal pain/discomfort (11.2%)
Metabolic/Nutritional | Increased weight >10 lb at 24 months (37.7%)
Nervous | Nervousness (10.8%); Dizziness (5.6%); Libido decreased (5.5%)
Reproductive (Urogenital) | Menstrual irregularities:; bleeding (57.3% at 12 months, 32.1% at 24 months) amenorrhea (55% at 12 months, 68% at 24 months)

Table 2. Adverse Reactions that Were Reported by between 1 and 5% of Subjects
Body System [Body System represented from COSTART medical dictionary.] | Adverse Reactions [Incidence (%)]
Body as a Whole | Asthenia/fatigue (4.2%); Backache (2.2%); Dysmenorrhea (1.7%); Hot flashes (1.0%)
Digestive | Nausea (3.3%); Bloating (2.3%)
Metabolic/Nutritional | Edema (2.2%)
Musculoskeletal | Leg cramps (3.7%); Arthralgia (1.0%)
Nervous | Depression (1.5%); Insomnia (1.0%)
Skin and Appendages | Acne (1.2%); No hair growth/alopecia (1.1%); Rash (1.1%)
Reproductive (Urogenital) | Leukorrhea (2.9%); Breast pain (2.8%); Vaginitis (1.2%)

Adverse reactions leading to study discontinuation in ≥2% of subjects: bleeding (8.2%), amenorrhea (2.1%), weight gain (2.0%).

6.2 Post-Marketing Experience

The following adverse reactions have been identified during post approval use of Depo-Provera CI. Because these reactions are reported voluntarily from a population of uncertain size, it is not always possible to reliably estimate their frequency or establish a causal relationship to drug exposure.

There have been cases of osteoporosis including osteoporotic fractures reported post-marketing in patients taking Depo-Provera CI.

Table 3. Adverse Reactions Reported during Post-Marketing Experience

Body System* | Adverse Reactions
Body as a Whole | Chest pain, Allergic reactions including angioedema, Fever, Injection site abscess†, Injection site infection†, Injection site nodule/lump, Injection site pain/tenderness, Injection site persistent atrophy/indentation/dimpling, Injection-site reaction, Lipodystrophy acquired, Chills, Axillary swelling
Cardiovascular | Syncope, Tachycardia, Thrombophlebitis, Deep vein thrombosis, Pulmonary embolus, Varicose veins
Digestive | Changes in appetite, Gastrointestinal disturbances, Jaundice, Excessive thirst, Rectal bleeding
Hematologic and Lymphatic | Anemia, Blood dyscrasia
Musculoskeletal | Osteoporosis
Neoplasms | Cervical cancer, Breast cancer
Nervous | Paralysis, Facial palsy, Paresthesia, Drowsiness
Respiratory | Dyspnea and asthma, Hoarseness
Skin and Appendages | Hirsutism, Excessive sweating and body odor, Dry skin, Scleroderma, Melasma, Chloasma
Reproductive (Urogenital*) | Lack of return to fertility, Unexpected pregnancy, Changes in breast size, Breast lumps or nipple bleeding, Galactorrhea, Increased libido, Uterine hyperplasia, Vaginal cysts, Genitourinary infections, Dyspareunia

* Body System represented from COSTART medical dictionary.
† Injection site abscess and injection site infections have been reported; therefore, strict aseptic injection technique should be followed when administering Depo‑Provera CI in order to avoid injection site infections [see Dosage and Administration (2.1)].

7 DRUG INTERACTIONS

7.1 Changes in Contraceptive Effectiveness Associated with Co-Administration of Other Products

If a woman on hormonal contraceptives takes a drug or herbal product that induces enzymes, including CYP3A4, that metabolize contraceptive hormones, counsel her to use additional contraception or a different method of contraception. Drugs or herbal products that induce such enzymes may decrease the plasma concentrations of contraceptive hormones, and may decrease the effectiveness of hormonal contraceptives. Some drugs or herbal products that may decrease the effectiveness of hormonal contraceptives include:

- barbiturates
- bosentan
- carbamazepine
- felbamate
- griseofulvin
- oxcarbazepine
- phenytoin
- rifampin
- St. John's wort
- topiramate

HIV protease inhibitors and non-nucleoside reverse transcriptase inhibitors: Significant changes (increase or decrease) in the plasma levels of progestin have been noted in some cases of co-administration of HIV protease inhibitors. Significant changes (increase or decrease) in the plasma levels of the progestin have been noted in some cases of co-administration with non-nucleoside reverse transcriptase inhibitors.

Antibiotics: There have been reports of pregnancy while taking hormonal contraceptives and antibiotics, but clinical pharmacokinetic studies have not shown consistent effects of antibiotics on plasma concentrations of synthetic steroids.

Consult the labeling of all concurrently-used drugs to obtain further information about interactions with hormonal contraceptives or the potential for enzyme alterations.

7.2 Laboratory Test Interactions

The pathologist should be advised of progestin therapy when relevant specimens are submitted.

The following laboratory tests may be affected by progestins including Depo-Provera CI:

(a) Plasma and urinary steroid levels are decreased (e.g., progesterone, estradiol, pregnanediol, testosterone, cortisol).
(b) Gonadotropin levels are decreased.
(c) Sex-hormone-binding-globulin concentrations are decreased.
(d) Protein-bound iodine and butanol extractable protein-bound iodine may increase. T3-uptake values may decrease.
(e) Coagulation test values for prothrombin (Factor II), and Factors VII, VIII, IX, and X may increase.
(f) Sulfobromophthalein and other liver function test values may be increased.
(g) The effects of medroxyprogesterone acetate on lipid metabolism are inconsistent. Both increases and decreases in total cholesterol, triglycerides, low-density lipoprotein (LDL) cholesterol, and high-density lipoprotein (HDL) cholesterol have been observed in studies.

8 USE IN SPECIFIC POPULATIONS

8.1 Pregnancy

Risk Summary

There is no use for contraception in pregnancy; therefore, Depo-Provera CI should be discontinued during pregnancy.

Epidemiologic studies and meta‑analyses have not found an increased risk of genital or non-genital birth defects (including cardiac anomalies and limb-reduction defects) following exposure to progestins before conception or during early pregnancy.

All pregnancies have a background risk of birth defect, loss, or other adverse outcomes. In the U.S. general population, the estimated background risk of major birth defects and miscarriage in clinically recognized pregnancies is 2-4% and 15-20%, respectively.

8.2 Lactation

Risk Summary

Although medroxyprogesterone acetate is detectable in the milk of mothers receiving Depo-Provera CI, milk composition, quality, and amount do not appear to be adversely affected. Effects on milk production and lactation initiation/duration remain unclear when administered before 6 weeks after delivery, therefore, in mothers who exclusively breastfeed, initiate Depo-Provera CI during or after the sixth post-partum week [see Dosage and Administration (2.1)].

No adverse effects in breastfed infants would be expected with maternal use of progestins. Neonates and infants exposed to medroxyprogesterone acetate from breast milk have been studied and no adverse effects have been noted.

The developmental and health benefits of breast-feeding should be considered along with the mother’s clinical need for Depo-Provera CI and any potential adverse effects on the breastfed child from Depo-Provera CI or from the underlying maternal condition.

8.3 Females and Males of Reproductive Potential

Depo-Provera CI is indicated for the prevention of pregnancy and would therefore be expected to impair female fertility until cessation of treatment. Women may experience a delay in return to ovulation and fertility (conception) following discontinuation of Depo-Provera CI [see Warnings and Precautions (5.15)].

8.4 Pediatric Use

Depo-Provera CI is not indicated before menarche. Use of Depo-Provera CI is associated with significant loss of BMD. This loss of BMD is of particular concern during adolescence and early adulthood, a critical period of bone accretion. In adolescents, interpretation of BMD results should take into account patient age and skeletal maturity. It is unknown if use of Depo-Provera CI by younger women will reduce peak bone mass and increase the risk of osteoporotic fractures in later life. Other than concerns about loss of BMD, the safety and effectiveness are expected to be the same for postmenarchal adolescents and adult women.

8.5 Geriatric Use

This product has not been studied in post-menopausal women and is not indicated in this population.

11 DESCRIPTION

Depo-Provera CI contains medroxyprogesterone acetate, a derivative of progesterone, as its active ingredient. Medroxyprogesterone acetate is active by the parenteral and oral routes of administration. It is a white to off‑white; odorless crystalline powder that is stable in air and that melts between 200°C and 210°C. It is freely soluble in chloroform, soluble in acetone and dioxane, sparingly soluble in alcohol and methanol, slightly soluble in ether, and insoluble in water.

The chemical name for medroxyprogesterone acetate is pregn-4-ene-3, 20-dione, 17-(acetyloxy)-6-methyl-, (6α-).

The structural formula is as follows:

Depo-Provera CI for IM injection is available in vials and prefilled syringes, each containing 1 mL of medroxyprogesterone acetate sterile aqueous suspension 150 mg/mL.

For Depo-Provera CI vials, each mL of sterile aqueous suspension contains:
Medroxyprogesterone acetate | 150 mg
Polyethylene glycol 3350 | 28.9 mg
Polysorbate 80 | 2.41 mg
Sodium chloride | 8.68 mg
Methylparaben | 1.37 mg
Propylparaben | 0.150 mg
Water for injection | quantity sufficient
When necessary, pH is adjusted with sodium hydroxide or hydrochloric acid, or both.

For Depo-Provera CI prefilled syringes, each mL of sterile aqueous suspension contains:
Medroxyprogesterone acetate | 150 mg
Polyethylene glycol 3350 | 28.5 mg
Polysorbate 80 | 2.37 mg
Sodium chloride | 8.56 mg
Methylparaben | 1.35 mg
Propylparaben | 0.147 mg
Water for injection | quantity sufficient
When necessary, pH is adjusted with sodium hydroxide or hydrochloric acid, or both.

12 CLINICAL PHARMACOLOGY

12.1 Mechanism of Action

Depo-Provera CI (medroxyprogesterone acetate [MPA]) inhibits the secretion of gonadotropins which primarily prevents follicular maturation and ovulation and causes thickening of cervical mucus. These actions contribute to its contraceptive effect.

12.2 Pharmacodynamics

No specific pharmacodynamic studies were conducted with Depo-Provera CI.

12.3 Pharmacokinetics

Absorption

Following a single 150 mg IM dose of Depo-Provera CI in eight women between the ages of 28 and 36 years old, medroxyprogesterone acetate concentrations, measured by an extracted radioimmunoassay procedure, increase for approximately 3 weeks to reach peak plasma concentrations of 1 to 7 ng/mL.

Distribution

Plasma protein binding of MPA averages 86%. MPA binding occurs primarily to serum albumin. No binding of MPA occurs with sex-hormone-binding globulin (SHBG).

Elimination

Metabolism

MPA is extensively metabolized in the liver by P450 enzymes. Its metabolism primarily involves ring A and/or side-chain reduction, loss of the acetyl group, hydroxylation in the 2-, 6-, and 21-positions or a combination of these positions, resulting in more than 10 metabolites.

Excretion

The concentrations of medroxyprogesterone acetate decrease exponentially until they become undetectable (<100 pg/mL) between 120 to 200 days following injection. Using an unextracted radioimmunoassay procedure for the assay of medroxyprogesterone acetate in serum, the apparent half-life for medroxyprogesterone acetate following IM administration of Depo-Provera CI is approximately 50 days. Most medroxyprogesterone acetate metabolites are excreted in the urine as glucuronide conjugates with only minor amounts excreted as sulfates.

Specific Populations

The effect of hepatic and/or renal impairment on the pharmacokinetics of Depo-Provera CI is unknown.

13 NONCLINICAL TOXICOLOGY

13.1 Carcinogenesis, Mutagenesis, Impairment of Fertility

[see Warnings and Precautions (5.3, 5.15) and Use in Specific Populations (8.3)].

14 CLINICAL STUDIES

14.1 Contraception

In five clinical studies using Depo-Provera CI, the 12-month failure rate for the group of women treated with Depo-Provera CI was zero (no pregnancies reported) to 0.7 by Life-Table method. The effectiveness of Depo‑Provera CI is dependent on the patient returning every 3 months (13 weeks) for reinjection.

14.2 Bone Mineral Density Changes in Women Treated with Depo-Provera CI

In a controlled, clinical study, adult women using Depo-Provera CI (150mg) for up to 5 years showed spine and hip bone mineral density (BMD) mean decreases of 5–6%, compared to no significant change in BMD in the control group. The decline in BMD was more pronounced during the first two years of use, with smaller declines in subsequent years. Mean changes in lumbar spine BMD of ‑2.86%, ‑4.11%, ‑4.89%, ‑4.93% and ‑5.38% after 1, 2, 3, 4, and 5 years, respectively, were observed. Mean decreases in BMD of the total hip and femoral neck were similar.

After stopping use of Depo-Provera CI, there was partial recovery of BMD toward baseline values during the 2-year post-therapy period. Longer duration of treatment was associated with less complete recovery during this 2-year period following the last injection. Table 4 shows the change in BMD in women after 5 years of treatment with Depo-Provera CI and in women in a control group, as well as the extent of recovery of BMD for the subset of the women for whom 2-year post treatment data were available.

Table 4. Mean Percent Change from Baseline in BMD in Adults by Skeletal Site and Cohort (5 Years of Treatment and 2 Years of Follow-Up)
Time in Study | Spine |  | Total Hip |  | Femoral Neck
 | Depo-Provera [The treatment group consisted of women who received Depo-Provera CI for 5 years and were then followed for 2 years post‑use (total time in study of 7 years).] | Control [The control group consisted of women who did not use hormonal contraception and were followed for 7 years.] | Depo-Provera | Control | Depo-Provera | Control
5 years | -5.38% n=33 | 0.43% n=105 | -5.16% n=21 | 0.19% n=65 | -6.12% n=34 | -0.27% n=106
7 years | -3.13% n=12 | 0.53% n=60 | -1.34% n=7 | 0.94% n=39 | -5.38% n=13 | -0.11% n=63

14.3 Bone Mineral Density Changes in Adolescent Females (12 to 18 Years of Age) Treated with Depo-Provera CI

The impact of Depo-Provera CI (150 mg) use for up to 240 weeks (4.6 years) was evaluated in an open-label non-randomized clinical study in 389 adolescent females (12 to 18 years of age). Use of Depo-Provera CI was associated with a significant decline from baseline in BMD.

Partway through the trial, drug administration was stopped (at 120 weeks). The mean number of injections per Depo-Provera CI user was 9.3. Table 5 summarizes the study findings. The decline in BMD at total hip and femoral neck was greater with longer duration of use. The mean decrease in BMD at 240 weeks was more pronounced at total hip (-6.4%) and femoral neck (-5.4%) compared to lumbar spine (-2.1%).

Adolescents in the untreated cohort had an increase in BMD during the period of growth following menarche. However, the two cohorts were not matched at baseline for age, gynecologic age, race, BMD and other factors that influence the rate of acquisition of BMD.

Table 5. BMD Mean Percent Change from Baseline in Adolescents Receiving ≥4 Injections per 60‑week Period, by Skeletal Site and Cohort
Duration of Treatment | Depo-Provera CI (150 mg IM) |  | Unmatched, Untreated Cohort
 | N | Mean % Change | N | Mean % Change
Total Hip BMD
Week 60 (1.2 years) | 113 | -2.75 | 166 | 1.22
Week 120 (2.3 years) | 73 | -5.40 | 109 | 2.19
Week 240 (4.6 years) | 28 | -6.40 | 84 | 1.71
Femoral Neck BMD
Week 60 | 113 | -2.96 | 166 | 1.75
Week 120 | 73 | -5.30 | 108 | 2.83
Week 240 | 28 | -5.40 | 84 | 1.94
Lumbar Spine BMD
Week 60 | 114 | -2.47 | 167 | 3.39
Week 120 | 73 | -2.74 | 109 | 5.28
Week 240 | 27 | -2.11 | 84 | 6.40

BMD Recovery Post-Treatment in Adolescents

Longer duration of treatment and smoking were associated with less recovery of BMD following the last injection of Depo-Provera CI. Table 6 shows the extent of recovery of BMD up to 60 months post-treatment for adolescents who received Depo-Provera CI for two years or less compared to more than two years. Post‑treatment follow-up showed that, in women treated for more than two years, only lumbar spine BMD recovered to baseline levels after treatment was discontinued. Adolescents treated with Depo-Provera CI for more than two years did not recover to their baseline BMD level at femoral neck and total hip even up to 60 months post-treatment. Adolescents in the untreated cohort gained BMD throughout the trial period (data not shown) [see Warnings and Precautions (5.1)].

Table 6. BMD Recovery (Months Post-Treatment) in Adolescents by Years of Depo‑Provera CI Use (2 Years or Less vs. More than 2 Years)
Duration of Treatment | 2 years or less |  | More than 2 years
 | N | Mean % Change from baseline | N | Mean % Change from baseline
Total Hip BMD
End of Treatment | 49 | -1.5% | 49 | -6.2%
12 M post-treatment | 33 | -1.4% | 24 | -4.6%
24 M post-treatment | 18 | 0.3% | 17 | -3.6%
36 M post-treatment | 12 | 2.1% | 11 | -4.6%
48 M post-treatment | 10 | 1.3% | 9 | -2.5%
60 M post-treatment | 3 | 0.2% | 2 | -1.0%
Femoral Neck BMD
End of Treatment | 49 | -1.6% | 49 | -5.8%
12 M post-treatment | 33 | -1.4% | 24 | -4.3%
24 M post-treatment | 18 | 0.5% | 17 | -3.8%
36 M post-treatment | 12 | 1.2% | 11 | -3.8%
48 M post-treatment | 10 | 2.0% | 9 | -1.7%
60 M post-treatment | 3 | 1.0% | 2 | -1.9%
Lumbar Spine BMD
End of Treatment | 49 | -0.9% | 49 | -3.5%
12 M post-treatment | 33 | 0.4% | 23 | -1.1%
24 M post-treatment | 18 | 2.6% | 17 | 1.9%
36 M post-treatment | 12 | 2.4% | 11 | 0.6%
48 M post-treatment | 10 | 6.5% | 9 | 3.5%
60 M post-treatment | 3 | 6.2% | 2 | 5.7%

14.4 Bone Fracture Incidence in Women Treated with Depo-Provera CI

A retrospective cohort study to assess the association between Depo-Provera CI injection and the incidence of bone fractures was conducted in 312,395 female contraceptive users in the UK. The incidence rates of fracture were compared between Depo-Provera CI users and contraceptive users who had no recorded use of Depo-Provera CI. The Incident Rate Ratio (IRR) for any fracture during the follow-up period (mean=5.5 years) was 1.41 (95% CI 1.35, 1.47). It is not known if this is due to Depo-Provera CI use or to other related lifestyle factors that have a bearing on fracture rate.

In the study, when cumulative exposure to Depo-Provera CI was calculated, the fracture rate in users who received fewer than 8 injections was higher than that in women who received 8 or more injections. However, it is not clear that cumulative exposure, which may include periods of intermittent use separated by periods of non-use, is a useful measure of risk, as compared to exposure measures based on continuous use.

There were very few osteoporotic fractures (fracture sites known to be related to low BMD) in the study overall, and the incidence of osteoporotic fractures was not found to be higher in Depo-Provera CI users compared to non-users.

Importantly, this study could not determine whether use of Depo-Provera CI has an effect on fracture rate later in life.

15 REFERENCES

1. Li CI, Beaber EF, Tang, MCT et al. Effect of Depo-Medroxyprogesterone Acetate on Breast Cancer Risk among Women 20 to 44 years of Age. Cancer Research 2012;72:2028–2035.
2. Paul C, Skegg DCG, Spears GFS. Depot medroxyprogesterone (Depo-Provera) and risk of breast cancer. Br Med J 1989; 299:759–62.

16 HOW SUPPLIED/STORAGE AND HANDLING

Depo-Provera CI is supplied in the following strengths and package configurations:

Package Configuration | Strength | NDC
Depo-Provera CI (medroxyprogesterone acetate sterile aqueous suspension 150 mg/mL)
1 mL vial | 150 mg/mL | NDC 0009-0746-30
25 × 1 mL vials | 150 mg/mL | NDC 0009-0746-35
Depo-Provera CI prefilled syringes packaged with 22 gauge × 1 1/2 inch Terumo® SurGuard™ Needles
1 mL prefilled syringe | 150 mg/mL | NDC 0009-7376-11

STORAGE AND HANDLING

Vials MUST be stored upright at controlled room temperature 20° to 25°C (68° to 77°F) [see USP].

17 PATIENT COUNSELING INFORMATION

Advise the patient to read the FDA‑approved patient labeling (Patient Information).

- Advise patients at the beginning of treatment that their menstrual cycle may be disrupted and that irregular and unpredictable bleeding or spotting results, and that this usually decreases to the point of amenorrhea as treatment with Depo-Provera CI continues, without other therapy being required.
- Counsel patients about the possible increased risk of breast cancer in women who use Depo-Provera CI [see Warnings and Precautions (5.3)].
- Counsel patients with a history of meningioma about the possible risk of worsening meningioma [see Warnings and Precautions (5.4)].
- Counsel patients that this product does not protect against HIV infection (AIDS) and other sexually transmitted infections.
- Counsel patients on Warnings and Precautions associated with use of Depo-Provera CI.
- Counsel patients to use a back-up method or alternative method of contraception when enzyme inducers are used with Depo-Provera CI.

This product's labeling may have been updated. For the most recent prescribing information, please visit www.pfizer.com.

To contact Pfizer’s Medical Information Department please visit www.pfizermedinfo.com or call 1‑800‑438‑1985.

LAB-0149-22.0

Patient Information

Depo-Provera® (DEP-po pro-VAIR-ah) CI
(medroxyprogesterone acetate injectable suspension)
Contraceptive Injection

Read this Patient Information carefully before you decide if Depo-Provera CI is right for you. This information does not take the place of talking with your gynecologist or other healthcare professional who specializes in women's health. If you have any questions about Depo-Provera CI, ask your healthcare professional. You should also learn about other birth control methods to choose the one that is best for you.

What is the most important information I should know about Depo-Provera CI?

Depo-Provera CI can cause serious side effects, including:

- Use of Depo-Provera CI may cause you to lose calcium stored in your bone and decrease your bone mass. The longer you use Depo-Provera CI, the greater your loss of calcium from your bones. Your bones may not recover completely when you stop using Depo-Provera CI.
- If you use Depo-Provera CI continuously for a long time (for more than 2 years), it may increase the risk of weak, porous bones (osteoporosis) that could increase the risk of broken bones, especially after menopause.
- You should not use Depo-Provera CI for more than two years unless you cannot use other birth control methods.
- It is not known if your risk of developing osteoporosis is greater if you are a teenager or young adult when you start to use Depo-Provera CI (see "What are the possible side effects of Depo-Provera CI?").

Depo-Provera CI is intended to prevent pregnancy. Depo-Provera CI does not protect against HIV infection (AIDS) and other sexually transmitted infections (STIs).

What is Depo-Provera CI?

Depo-Provera CI is a progestin hormone birth control method that is given by injection (a shot) to prevent pregnancy.

How well does Depo-Provera CI work?

Your chance of getting pregnant depends on how well you follow the directions for taking your Depo-Provera CI. The more carefully you follow the directions (such as returning every 3 months for your next injection), the less chance you have of getting pregnant.

In clinical studies, about 1 out of 100 women got pregnant during the first year that they used Depo-Provera CI.

The following chart shows the chance of getting pregnant for women who use different methods of birth control. Each box on the chart contains a list of birth control methods that are similar in effectiveness. The most effective methods are at the top of the chart. The box on the bottom of the chart shows the chance of getting pregnant for women who do not use birth control and are trying to get pregnant.

How should I take Depo-Provera CI?

- Depo-Provera CI is given by your healthcare professional as a shot into your muscle (intramuscular injection). The shot is given in your buttock or upper arm 1 time every 3 months. At the end of the 3 months, you will need to return to your healthcare professional for your next injection in order to continue your protection against pregnancy.
- To make sure that you are not pregnant before you take Depo-Provera CI, the first injection should be given only:
  - during the first 5 days of a normal menstrual period, or
  - within the first 5 days after giving birth, if you are not breastfeeding, or
  - at the 6th week after giving birth, if you are feeding your baby only breastmilk.
- Depo-Provera CI may be given at other times than those listed above, but you will likely need to have a pregnancy test first to show that you are not pregnant.
- During treatment with Depo-Provera CI, you should see your healthcare professional every year for a blood pressure check and other healthcare needs.

Who Should Not Use Depo-Provera CI?

Do not use Depo-Provera CI if you:

- have bleeding from your vagina that has not been explained
- have breast cancer now or in the past, or think you have breast cancer
- have had a stroke
- ever had blood clots in your arms, legs or lungs
- have problems with your liver or liver disease
- are allergic to medroxyprogesterone acetate or any of the other ingredients in Depo-Provera CI. See the end of this leaflet for a complete list of ingredients in Depo-Provera CI.

What should I tell my healthcare professional before taking Depo-Provera CI?

Before taking Depo-Provera CI, tell your healthcare professional if you have:

- risk factors for weak bones (osteoporosis) such as bone disease, use alcohol or smoke regularly, anorexia nervosa, or a strong family history of osteoporosis
- irregular or lighter than usual menstrual periods
- breast cancer now or in the past, or think you have breast cancer
- a family history of breast cancer
- an abnormal mammogram (breast X-ray), lumps in your breasts, or bleeding from your nipples
- have or have ever had a type of usually benign brain tumor called a meningioma
- kidney problems
- high blood pressure
- had a stroke
- had blood clots in your arms, legs or lungs
- migraine headaches
- asthma
- epilepsy (convulsions or seizures)
- diabetes
- depression or a history of depression
- any other medical conditions

If you are breastfeeding or plan to breastfeed, Depo-Provera CI can pass into your breast milk. Talk to your healthcare professional about the best way to feed your baby if you take Depo-Provera CI.

Tell your healthcare professional about all of the medicines you take, including prescription and nonprescription medicines, vitamins, and herbal supplements.

Depo-Provera CI and certain other medicines may affect each other, causing serious side effects. Sometimes the doses of other medicines may need to be changed while you are taking Depo-Provera CI.

Some medicines may make Depo-Provera CI less effective at preventing pregnancy, including those listed below.

Especially tell your healthcare professional if you take:

- medicine to help you sleep
- bosentan
- medicine for seizures
- griseofulvin
- an antibiotic
- medicine for HIV (AIDS)
- St. John's wort

Know the medicines you take. Keep a list of your medicines with you to show your healthcare professional or pharmacist before you first start taking Depo-Provera CI or when you get a new medicine.

Follow your healthcare professional's instructions about using a back-up method of birth control if you are taking medicines that may make Depo-Provera CI less effective.

What are the possible side effects of Depo-Provera CI?

Depo-Provera CI can cause serious side effects, including:

- Effect on the bones: See "What is the most important information I should know about Depo-Provera CI?".
  Teenage years are the most important years to gain bone strength. The decrease in calcium in your bones is of most concern if you are a teenager or have the following problems:
  - bone disease
  - an eating disorder (anorexia nervosa)
  - a strong family history of osteoporosis
  - you take a drug that can lower the amount of calcium in your bones (drugs for epilepsy or steroid drugs)
  - you drink a lot of alcohol (more than 2 drinks a day)
  - you smoke
If you need a birth control method for more than 2 years, your healthcare professional may switch you to another birth control method instead of using Depo-Provera CI. If you continue using Depo-Provera CI, your healthcare professional may ask you to have a bone test, especially if you have other risks for weak bones.
When Depo-Provera CI is stopped, your bones may start to regain calcium. However, in a study of teenage girls who used Depo-Provera CI for more than 2 years, their hip bones did not completely recover by 5 years after they stopped using Depo-Provera CI. Taking calcium and Vitamin D and exercising daily may lessen the loss of calcium from your bones.
- possible increased risk of breast cancer. Women who use Depo-Provera CI may have a slightly increased risk of breast cancer compared to non-users.
- blood clots in your arms, legs, lungs, and eyes
- stroke
- a pregnancy outside of your uterus (ectopic pregnancy). Ectopic pregnancy is a medical emergency that often requires surgery. Ectopic pregnancy can cause internal bleeding, infertility, and even death.
- allergic reactions. Severe allergic reactions have been reported in some women using Depo-Provera CI.
- loss of vision or other eye problems
- migraine headaches
- possible increased risk for growth of a meningioma (a usually benign brain tumor), primarily when the product is used for a long time.
- depression
- convulsions or seizures
- liver problems

Call your healthcare professional right away if you have:

- sharp chest pain, coughing up blood, or sudden shortness of breath (indicating a possible clot in the lung)
- sudden severe headache or vomiting, dizziness or fainting, problems with your eyesight or speech, weakness, or numbness in an arm or leg (indicating a possible stroke)
- severe pain or swelling in the calf (indicating a possible clot in the leg)
- sudden blindness, partial or complete (indicating a possible clot in the blood vessels of the eye)
- unusually heavy vaginal bleeding
- severe pain or tenderness in the lower abdominal area
- persistent pain, pus, or bleeding at the injection site
- yellowing of the eyes or skin
- hives
- difficulty breathing
- swelling of the face, mouth, tongue or neck

The most common side effects of Depo-Provera CI include:

- irregular vaginal bleeding, such as lighter or heavier menstrual bleeding, or continued spotting
- weight gain. You may experience weight gain while you are using Depo-Provera CI. About two-thirds of the women who used Depo-Provera CI in the clinical trials reported a weight gain of about 5 pounds during the first year of use. You may continue to gain weight after the first year. Women who used Depo-Provera CI for 2 years gained an average of 8 pounds over those 2 years.
- abdominal pain
- headache
- weakness
- tiredness
- nervousness
- dizziness

Tell your healthcare professional if you have any side effect that bothers you or does not go away.

These are not all the possible side effects of Depo-Provera CI. For more information, ask your healthcare professional or pharmacist.

Call your doctor for medical advice about side effects. You may report side effects to FDA at 1- 800-FDA-1088.

What other information should I know before choosing Depo-Provera CI?

- Pregnancy. When you take Depo-Provera CI every 3 months, your chance of getting pregnant is very low. You could miss a period or have a light period and not be pregnant. If you miss 1 or 2 periods and think you might be pregnant, see your healthcare professional as soon as possible. You should not use Depo-Provera CI if you are pregnant. However, Depo-Provera CI taken by accident during pregnancy does not seem to cause birth defects.
- Nursing Mothers. Although Depo-Provera CI can be passed to the nursing baby in the breast milk, no harmful effects on babies have been found. Depo-Provera CI does not stop the breasts from producing milk, so it can be used by nursing mothers. However, to minimize the amount of Depo-Provera CI that is passed to the baby in the first weeks after birth, you should wait until your baby is 6 weeks old before you start using Depo-Provera CI for birth control.

How will Depo-Provera CI change my periods?

- Change in normal menstrual cycle. The side effect reported most frequently by women who use Depo-Provera CI for birth controls is a change in their normal menstrual cycle. During the first year of using Depo-Provera CI, you might have one or more of the following changes:
  - irregular or unpredictable bleeding or spotting
  - an increase or decrease in menstrual bleeding
  - no bleeding at all. In clinical studies of Depo-Provera CI, 55% of women reported no menstrual bleeding (amenorrhea) after one year of use and 68% of women reported no menstrual bleeding after two years of use.
- Missed period. During the time you are using Depo-Provera CI for birth controls, you may skip a period, or your periods may stop completely. If you have been receiving your shot of Depo-Provera CI regularly every 3 months, then you are probably not pregnant. However, if you think that you may be pregnant, see your healthcare professional.

Unusually heavy or continuous bleeding is not a usual effect of Depo-Provera CI and if this happens you should see your healthcare professional right away.

With continued use of Depo-Provera CI, bleeding usually decreases and many women stop having periods completely. When you stop using Depo-Provera CI your menstrual period will usually, in time, return to its normal cycle.

What if I want to become pregnant?

Because Depo-Provera CI is a long-acting birth control method, it takes some time after your last shot for its effect to wear off. Most women who try to get pregnant after using Depo-Provera CI get pregnant within 18 months after their last shot. The length of time you use Depo-Provera CI has no effect on how long it takes you to become pregnant after you stop using it.

General Information about Depo-Provera CI

Medicines are sometimes prescribed for conditions that are not mentioned in patient information leaflets. This leaflet summarizes the most important information about Depo-Provera CI. If you would like more information, talk with your healthcare professional. You can ask your healthcare professional for information about Depo-Provera CI that is written for healthcare professionals.

What are the ingredients in Depo-Provera CI?

Active ingredient: medroxyprogesterone acetate

Inactive ingredients: polyethylene glycol 3350, polysorbate 80, sodium chloride, methylparaben, propylparaben, and water for injection. When necessary, pH is adjusted with sodium hydroxide or hydrochloric acid, or both.

This Patient Information has been approved by the U.S. Food and Drug Administration.

This product's labeling may have been updated. For the most recent prescribing information, please visit www.pfizer.com.

LAB-0148-15.0

Revised December 2025

PRINCIPAL DISPLAY PANEL - 150 mg/mL Vial Label

NDC 0009-0746-30
Rx only

Depo-Provera®
Contraceptive
Injection

medroxyPROGESTERone acetate
injectable suspension, USP

150 mg/mL

PRINCIPAL DISPLAY PANEL - 150 mg/mL Vial Carton

Pfizer

NDC 0009-0746-30
Rx only

Depo-Provera®
Contraceptive
Injection

medroxyPROGESTERone
acetate injectable
suspension, USP

150 mg/mL

1 mL Single-Dose Vial

For intramuscular use only

PRINCIPAL DISPLAY PANEL - 1 mL Syringe Label

Pfizer
NDC 0009-7376-11
Rx only

Depo-Provera®
Contraceptive Injection

150 mg per mL

medroxyprogesterone acetate
injectable suspension, USP

Intramuscular use only
1 mL Single Dose Syringe
Shake vigorously before use
Pfizer Inc, New York, NY 10001
LOT/EXP
PAA234178

PRINCIPAL DISPLAY PANEL - 1 mL Syringe Carton - NDC 0009-7376-11

NDC 0009-7376-11

Pfizer
Depo-Provera® Contraceptive Injection
(medroxyprogesterone acetate) injectable suspension, USP

150 mg per mL

Intramuscular use only
Rx only
Single Use Syringe

1 mL Prefilled Syringe